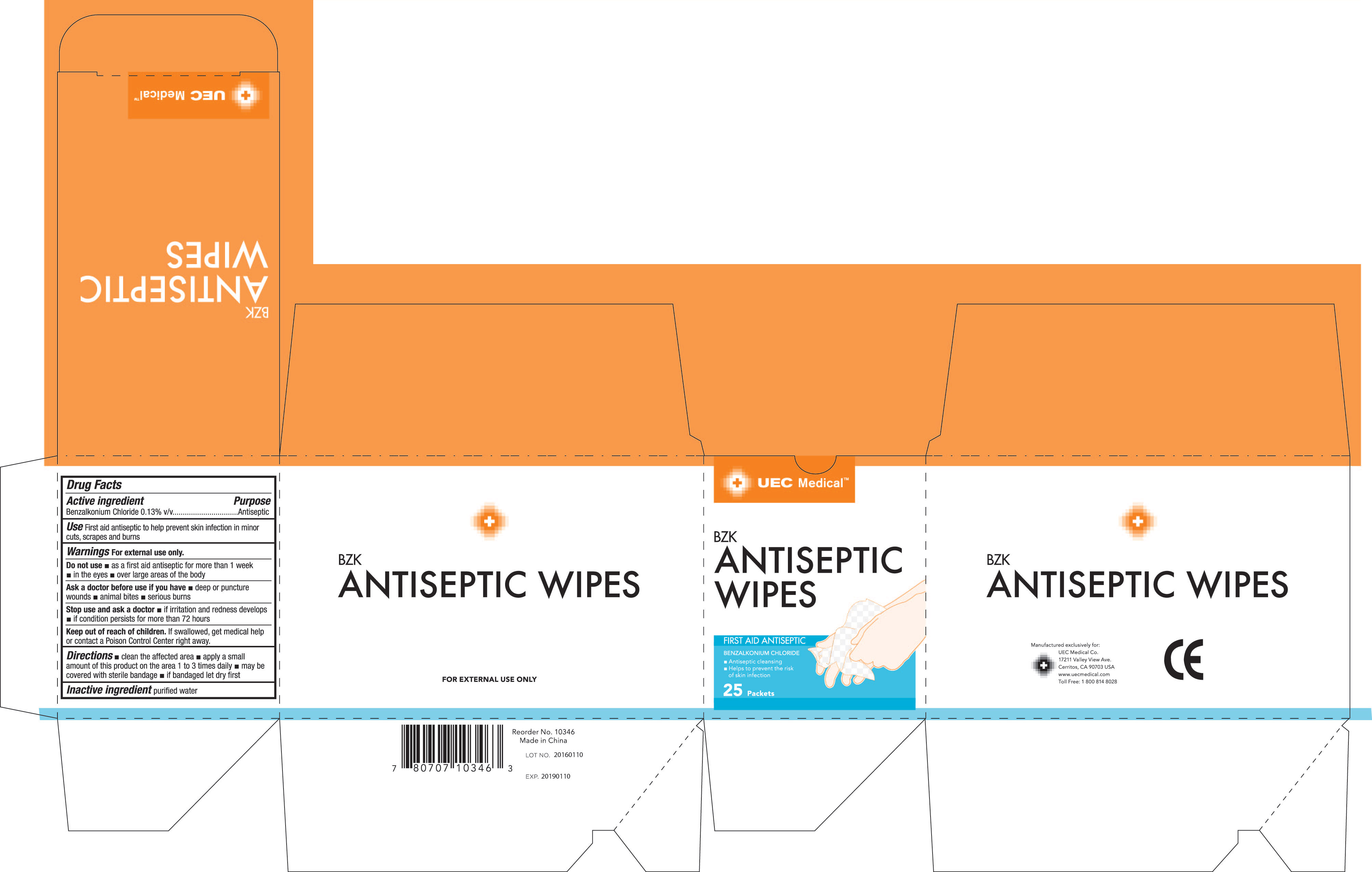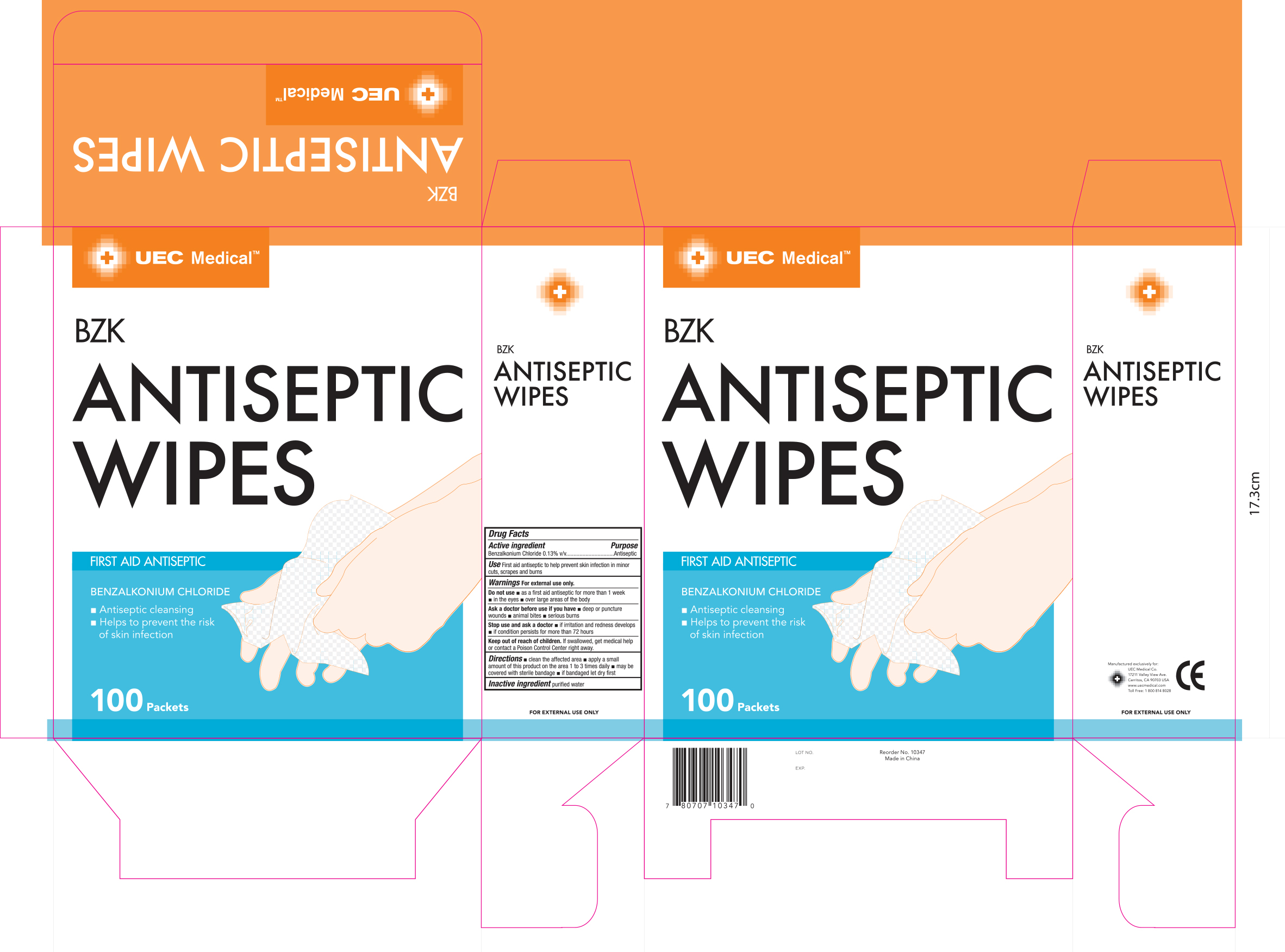 DRUG LABEL: UEC Medical BZK Antiseptic Wipes
NDC: 65923-345 | Form: CLOTH
Manufacturer: United Exchange Corp.
Category: otc | Type: HUMAN OTC DRUG LABEL
Date: 20170310

ACTIVE INGREDIENTS: BENZALKONIUM CHLORIDE 0.13 g/100 g
INACTIVE INGREDIENTS: WATER

Active ingredient Purpose

Benzalkonium Chloride 0.13% v/v....................Antiseptic

Use

First aid antiseptic to help prevent skin infection in minor cuts, scrapes and burns

Warnings For external use only.

Do not use

- as a first aid antiseptic for more than 1 week
- in the eyes
- over large areas of the body

Ask a doctor before use if you have

- deep or puncture wounds
- animal bites
- serious burns

Stop use and ask a doctor

- if irritation and redness develops
- if condition persists for more than 72 hours

Keep out of reach of children. If swallowed, get medical help or contact a Poison Control Center right away.

Directions

- clean the affected area
- apply a small amount of this product on the area 1 to 3 times daily
- may be covered with sterile bandage
- if bandaged let dry first

Inactive ingredient purified water

DOSAGE AND ADMINISTRATION

Manufactured exclusively for:

UEC Medical Co.

17211 Valley View Ave.

Cerritos, CA 90703 USA

www.uecmedical.com